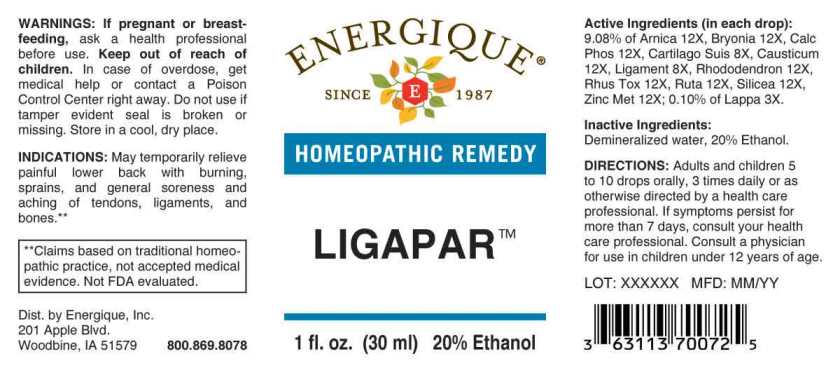 DRUG LABEL: Ligapar
NDC: 44911-0477 | Form: LIQUID
Manufacturer: Energique, Inc.
Category: homeopathic | Type: HUMAN OTC DRUG LABEL
Date: 20240422

ACTIVE INGREDIENTS: ARCTIUM LAPPA ROOT 3 [hp_X]/1 mL; HUMAN LIGAMENT 8 [hp_X]/1 mL; SUS SCROFA CARTILAGE 8 [hp_X]/1 mL; ARNICA MONTANA WHOLE 12 [hp_X]/1 mL; BRYONIA ALBA ROOT 12 [hp_X]/1 mL; TRIBASIC CALCIUM PHOSPHATE 12 [hp_X]/1 mL; CAUSTICUM 12 [hp_X]/1 mL; RHODODENDRON AUREUM LEAF 12 [hp_X]/1 mL; TOXICODENDRON PUBESCENS LEAF 12 [hp_X]/1 mL; RUTA GRAVEOLENS FLOWERING TOP 12 [hp_X]/1 mL; SILICON DIOXIDE 12 [hp_X]/1 mL; ZINC 12 [hp_X]/1 mL
INACTIVE INGREDIENTS: WATER; ALCOHOL

DRUG FACTS:

ACTIVE INGREDIENTS:

(in each drop): 9.08% of Arnica Montana 12X, Bryonia (Alba) 12X, Calcarea Phosphorica 12X, Cartilago Suis 8X, Causticum 12X, Ligament (Suis) 8X, Rhododendron Chrysanthum 12X, Rhus Tox 12X, Ruta Graveolens 12X, Silicea 12X, Zincum Metallicum 12X; 0.10% of Lappa Major 3X.

INDICATIONS:

May temporarily relieve painful lower back with burning, sprains, and general soreness and aching of tendons, ligaments and bones.**

**Claims based on traditional homeopathic practice, not accepted medical evidence. Not FDA evaluated.

WARNINGS:

If pregnant or breast-feeding, ask a health professional before use.

Keep out of reach of children. In case of overdose, get medical help or contact a Poison Control Center right away.

Do not use if tamper evident seal is broken or missing.

Store in a cool, dry place.

KEEP OUT OF REACH OF CHILDREN:

In case of overdose, get medical help or contact a Poison Control Center right away.

DIRECTIONS:

Adults and children 5 to 10 drops orally, 3 times daily or as otherwise directed by a health care professional. If symptoms persist for more than 7 days, consult your health care professional.

Consult a physician for use in children under 12 years of age.

INDICATIONS:

May temporarily relieve painful lower back with burning, sprains, and general soreness and aching of tendons, ligaments and bones.**

**Claims based on traditional homeopathic practice, not accepted medical evidence. Not FDA evaluated.

INACTIVE INGREDIENTS:

Demineralized water, 20% Ethanol.

QUESTIONS:

Dist. by Energique, Inc.

201 Apple Blvd.

Woodbine, IA 51579 800.869.8078

PACKAGE LABEL DISPLAY:

ENERGIQUE

SINCE 1987

HOMEOPATHIC REMEDY

LIGAPAR

1 fl. oz. (30 ml)